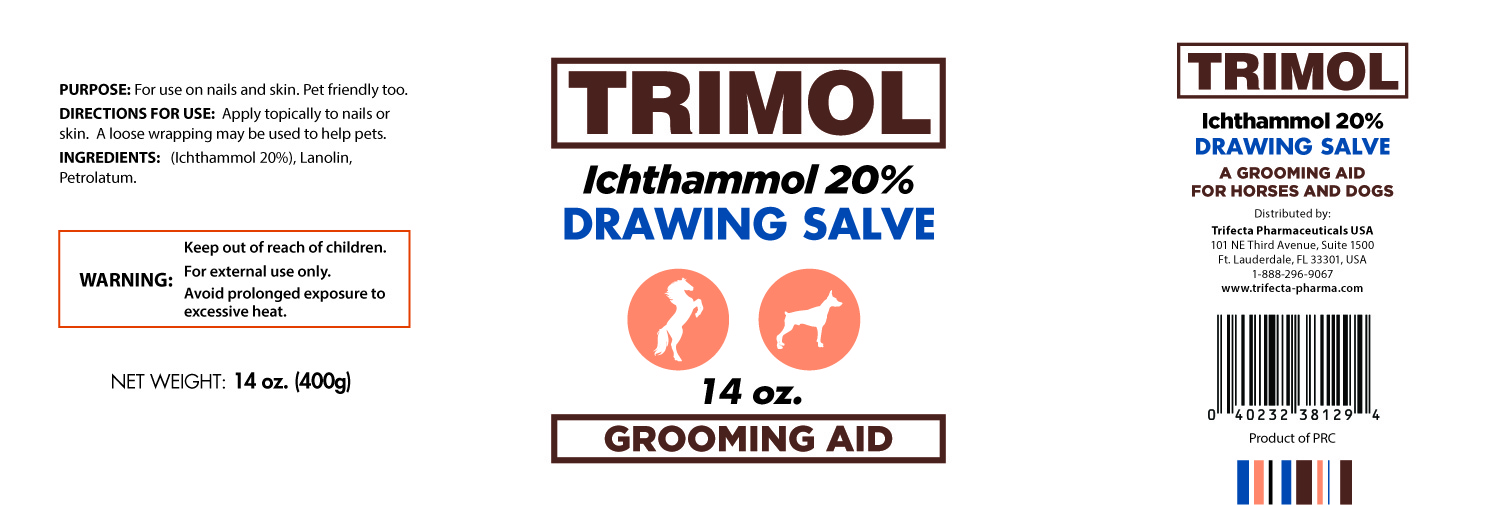 DRUG LABEL: TRIMOL
NDC: 69396-010 | Form: SALVE
Manufacturer: Trifecta Pharmaceuticals USA LLC
Category: homeopathic | Type: HUMAN OTC DRUG LABEL
Date: 20241231

ACTIVE INGREDIENTS: ICHTHAMMOL 20 g/100 g
INACTIVE INGREDIENTS: PETROLATUM; LANOLIN

TRIMOL

Active Ingredient

Ichthammol 20%

Purpose

For use on skin abraisions or sores

Warnings

For External Use only.

Directions:

Apply topically to affected parts once or twice a day. A loose wrapping may be applied. Avoid prolonged exposure to excessive heat.

Inactive Ingredients

Lanolin, Petrolatum

A GROOMING AID FOR HORSES AND DOGS

Distributed by:

Trifecta Pharmaceuticals USA

101 NE Third Avenue, Suite 1500

Fort Lauderdale, FL. 33301 USA

1-888-296-9067

www.trifecta-pharma.com

Uses:

Use on skin and nails